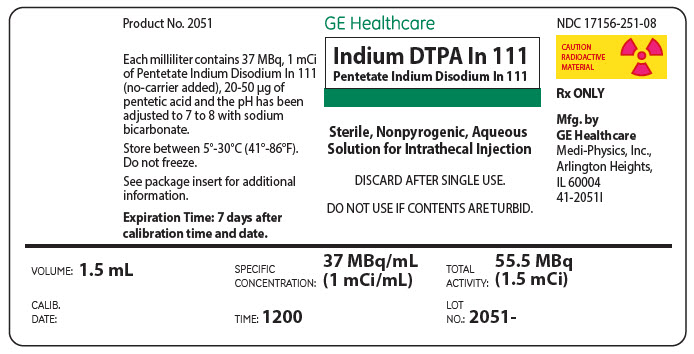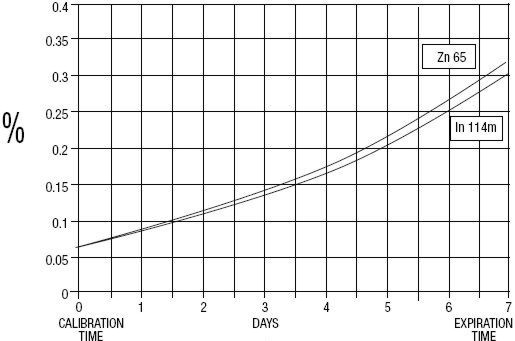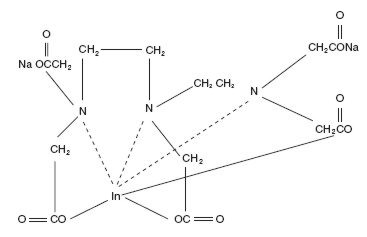 DRUG LABEL: Indium DTPA In 111
NDC: 17156-251 | Form: SOLUTION
Manufacturer: Medi-Physics, Inc. dba GE Healthcare
Category: prescription | Type: HUMAN PRESCRIPTION DRUG LABEL
Date: 20240110

ACTIVE INGREDIENTS: Indium In-111 Pentetate Disodium 1 mCi/1 mL
INACTIVE INGREDIENTS: Pentetic Acid; Sodium Bicarbonate

INDIUM DTPA In 111
Pentetate Indium Disodium In 111

Rx ONLY

DESCRIPTION

GE Healthcare (Medi-Physics, Inc.) Indium DTPA In 111 is a diagnostic drug for intrathecal use. It is available as a sterile, pyrogen-free, isotonic, aqueous solution, buffered to pH 7 to 8. At calibration time, each milliliter contains 37 MBq, 1 mCi of Pentetate Indium Disodium In 111 (no-carrier-added), 20 to 50 µg of pentetic acid, and sodium bicarbonate for pH adjustment. The drug is to be discarded after single use. Radionuclidic purity at calibration time is at least 99.88% with less than 0.06% Indium In 114m and 0.06% Zinc Zn 65. The concentration of each radionuclidic contaminant changes with time. Graph 1 shows maximum concentration of each radionuclidic impurity as a function of time.

Graph 1 - Radionuclidic Impurities

The chemical names are 1. Indate(2-)-^111 In-[N,N-bis[2-[bis-(carboxymethyl)amino]ethyl]glycinato(5-)]-disodium; and 2. Disodium [N,N-bis[2-(carboxymethyl)amino]glycinato(5-)]-indate (2-)^111In.

Molecular formula: C14H18O10N3 ^111In Na2

Molecular weight: 545.29

Structural formula:

PHYSICAL CHARACTERISTICS

Indium 111 decays by electron capture with a physical half-life of 67.9 hours. The energies of the photons that are useful for detection and imaging studies are listed in Table 1.

Table 1. Principal Radiation Emission Data [Kocher, David C.,"Radioactive Decay Data Tables,"DOE/TIC-11026, 115, (1981).]
Radiation | Mean %/Disintegration | Mean Energy (keV)
Gamma-2 | 90.2 | 171.3
Gamma-3 | 94.0 | 245.4

EXTERNAL RADIATION

The specific gamma ray constant for Indium In 111 is 3.3 R/hr-mCi at 1 cm. The half-value thickness of lead (Pb) for Indium In 111 is 0.021 cm. To facilitate control of the radiation exposure from millicurie amounts of this radionuclide, a range of values for the relative attenuation of the radiation emitted by this radionuclide that results from interposition of various thicknesses of Pb is shown in Table 2. For example, the use of a 0.8 cm thickness of Pb will attenuate the radiation emitted by a factor of about 1,000.

Table 2. Radiation Attenuation by Lead Shielding
Shield Thickness (Pb) cm | Coefficient of Attenuation
0.021 | 0.5
0.19 | 10^-1
0.49 | 10^-2
0.80 | 10^-3
1.1 | 10^-4
To correct for physical decay of this radionuclide, the fractions that remain at selected time intervals after the time of calibration are shown in Table 3.

Table 3. Physical Decay Chart: Indium In 111, Half-Life 67.9 Hours
Hours | Fraction Remaining | Hours | Fraction Remaining
0 [Calibration Time] | 1.000 | 84 | 0.424
12 | 0.885 | 96 | 0.375
24 | 0.783 | 108 | 0.332
36 | 0.693 | 120 | 0.294
48 | 0.613 | 132 | 0.260
60 | 0.542 | 144 | 0.230
72 | 0.480 | 168 | 0.180

CLINICAL PHARMACOLOGY

After intrathecal administration, the radiopharmaceutical is absorbed from the subarachnoid space as described below, and the remainder flows superiorly to the basal cisterns within 2 to 4 hours and subsequently will be apparent in the Sylvian cisterns, the interhemispheric cisterns, and over the cerebral convexities. In normal individuals, the radiopharmaceutical will have ascended to the parasagittal region within 24 hours with simultaneous partial or complete clearance of activity from the basal cisterns and Sylvian regions. In contrast to air, the radiopharmaceutical does not normally enter the cerebral ventricles.

Although the primary absorption of cerebrospinal fluid (CSF) into the blood stream occurs at the arachnoid villi, there is some evidence that a significant fraction of CSF is also absorbed across both the cerebral and spinal leptomeninges. Lesser quantities may also be absorbed across the ventricular ependyma. It is also generally held that these alternate routes of CSF absorption may assume primary importance when the major routes of the flow are pathologically obstructed. Approximately 65% of the administered dose is excreted by the kidneys within 24 hours and this increases to 85% in 72 hours.

INDICATIONS AND USAGE

Pentetate Indium Disodium In 111 is recommended for use in radionuclide cisternography.

CONTRAINDICATIONS

None known.

WARNINGS

The contents of the vial are radioactive. Adequate shielding of the preparation must be maintained at all times.

Since the drug is excreted by the kidneys, caution should be exercised in patients with severely impaired renal function.

PRECAUTIONS

General

Pentetate Indium Disodium In 111, as well as other radioactive drugs, must be handled with care and appropriate safety measures should be used to minimize external radiation exposure to clinical personnel, and to minimize radiation exposure to patients consistent with proper patient management.

Radiopharmaceuticals should be used only by physicians who are qualified by training and experience in the safe use and handling of radionuclides, and whose experience and training have been approved by the appropriate government agency authorized to license the use of radionuclides.

Do not use after the expiration time and date (7 days after calibration time and date stated on the label).

Discard vial after a single use. Do not use if contents are turbid.

Carcinogenesis, Mutagenesis, Impairment of Fertility

No long-term animal studies have been performed to evaluate carcinogenic potential, mutagenic potential, or whether Pentetate lndium Disodium In 111 affects fertility in males or females.

Pregnancy Category C

Animal reproduction studies have not been conducted with GE Healthcare (Medi-Physics, Inc.) Indium DTPA In 111. Also, it is not known whether Pentetate Indium Disodium In 111 can cause fetal harm when administered to a pregnant woman or can affect reproduction capacity. Pentetate Indium Disodium In 111 should be given to a pregnant woman only if clearly needed.

Ideally, examinations using radiopharmaceuticals, especially those elective in nature, of a woman of childbearing capability should be performed during the first few (approximately 10) days following the onset of menses.

Nursing Mothers

It is not known whether this drug is excreted in human milk. Because many drugs are excreted in human milk, formula feedings should be substituted for breast feedings when Pentetate Indium Disodium In 111 is administered to a nursing mother.

Pediatric Use

Safety and effectiveness in pediatric patients have not been established.

Geriatric use

Clinical studies of Indium DTPA In 111 did not include sufficient numbers of subjects aged 65 and over to determine whether they respond differently from younger subjects. Other reported clinical experience has not identified differences in responses between the elderly and younger patients. In general, dose selection for an elderly patient should be cautious, usually starting at the low end of the dosing range, reflecting the greater frequency of decreased hepatic, renal, or cardiac function, and of concomitant disease or other drug therapy.

The drug is known to be substantially excreted by the kidney, and the risk of toxic reactions to this drug may be greater in patients with impaired renal function. Because elderly patients are more likely to have decreased renal function, care should be taken in dose selection, and it may be useful to monitor renal function.

ADVERSE REACTIONS

Aseptic meningitis and pyrogenic reactions have been rarely (less than 0.4%) observed following cisternography with Pentetate lndium Disodium In 111.

One death has been reported to have occurred within 20 minutes following the administration of Pentetate Indium Disodium In 111 and appears to be drug related. In addition, two cases of septic meningitis have also been reported. There have also been reports of skin reactions and vomiting following administration of Pentetate lndium Disodium In 111. Relationship of the drug to these latter occurrences has not been established.

DOSAGE AND ADMINISTRATION

Extreme care must be exercised to assure aseptic conditions in intrathecal injections.

The maximum recommended intrathecal dose in the average patient (70 kg) is 18.5 MBq, 500 µCi. The patient dose should be measured by a suitable radioactivity calibration system immediately prior to administration.

Parenteral drug products should be inspected visually for particulate matter and discoloration prior to administration whenever solution and container permit.

RADIATION DOSIMETRY

The estimated absorbed radiation doses to selected organs of an average (70 kg) patient from intrathecal administration of a maximum dose of 18.5 MBq, 500 µCi of Pentetate Indium Disodium In 111 are shown in Table 4.

Table 4. Absorbed Radiation Dose [Method of Calculation: "S" Absorbed Dose per Unit Cumulated Activity for Selected Radionuclides and Organs, MIRD Pamphlet No. 11, 1975.]
Organ | mGy/18.5 MBq | rads/500 µCi
Total Body | 0.41 | 0.041
Kidneys | 2.2 | 0.22
Spinal Cord
Surface | 50.0 | 5.0
Average | 15.0 | 1.5
Brain
Surface | 41.0 | 4.1
Average | 4.0 | 0.4
Bladder
2-hour void | 2.1 | 0.21
4.8-hour void | 5.0 | 0.5
Testes
2-hour void | 0.4 | 0.04
4.8-hour void | 0.5 | 0.05
Ovaries
2-hour void | 0.6 | 0.06
4.8-hour void | 0.6 | 0.06

HOW SUPPLIED

Pentetate Indium Disodium In 111 (no-carrier-added) is supplied in single-dose glass vials, each containing 1.5 mL of solution with a concentration of 37 MBq, 1 mCi per mL and a total activity of 55.5 MBq, 1.5 mCi per vial at calibration time. Vials are packaged in individual lead shields with plastic outer containers.

NDC 17156-251-08

Storage

Store vial in its lead shield at a temperature of 5°-30°C (41°-86°F). Do not freeze.

Disposal

The residual materials may be discarded in ordinary trash provided the vials and syringes read no greater than background with an appropriate low-range survey meter. All identifying labels should be destroyed before discarding.

This radiopharmaceutical is licensed by Illinois Emergency Management Agency for distribution to persons licensed pursuant to 32 III. Adm. Code 330.260(a) and Part 335, Subpart E, 335.4010, or under equivalent licenses of an Agreement State or a Licensing State.

Product Number: 2051

GE Healthcare
Medi-Physics, Inc.
3350 North Ridge Avenue
Arlington Heights, IL 60004

GE and the GE Monogram are trademarks of General Electric Company.

43-2051G

Revised February 2020

PRINCIPAL DISPLAY PANEL - 1.5 mL Vial Label

GE Healthcare

Indium DTPA In 111
Pentetate Indium Disodium In 111

Sterile, Nonpyrogenic, Aqueous
Solution for Intrathecal Injection

DISCARD AFTER SINGLE USE.

DO NOT USE IF CONTENTS ARE TURBID.

VOLUME: 1.5 mL

SPECIFIC
CONCENTRATION:
37 MBq/mL
(1 mCi/mL)

TOTAL
ACTIVITY:
55.5 MBq
(1.5 mCi)

CALIB.
DATE:

TIME: 1200

LOT
NO.:
2051 –